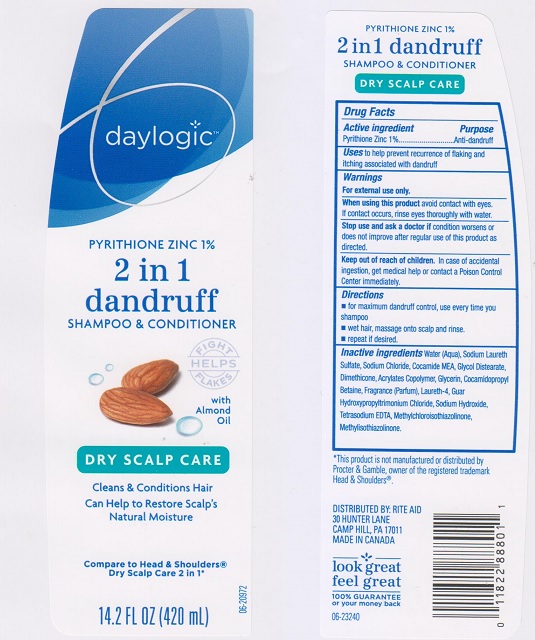 DRUG LABEL: Daylogic 2in1 Dandruff Dry Scalp Care
NDC: 11822-4251 | Form: LIQUID
Manufacturer: Rite Aid Corporation
Category: otc | Type: HUMAN OTC DRUG LABEL
Date: 20170607

ACTIVE INGREDIENTS: PYRITHIONE ZINC 10 mg/1 mL
INACTIVE INGREDIENTS: WATER; SODIUM LAURETH SULFATE; SODIUM CHLORIDE; COCO MONOETHANOLAMIDE; GLYCOL DISTEARATE; DIMETHICONE; METHACRYLIC ACID - METHYL METHACRYLATE COPOLYMER (1:1); GLYCERIN; COCAMIDOPROPYL BETAINE; LAURETH-4; GUAR HYDROXYPROPYLTRIMONIUM CHLORIDE (1.7 SUBSTITUENTS PER SACCHARIDE); SODIUM HYDROXIDE; EDETATE SODIUM; METHYLCHLOROISOTHIAZOLINONE; METHYLISOTHIAZOLINONE

Drug Facts

Active ingredient

Pyrithione Zinc 1%

Purpose

Anti-dandruff

Uses

to help prevent recurrence of flaking and itching associated with dandruff

Warnings

For external use only.

When using this product

avoid contact with eyes. If contact occurs, rinse eyes thoroughly with water.

Stop use and ask a doctor if

condition worsens or does not improve after regular use of this product as directed.

Keep out of reach of children.

In case of accidental ingestion, get medical help or contact a Poison Control Center immediately.

Directions

- for maximum dandruff control, use every time you shampoo.
- wet hair, massage onto scalp and rinse.
- repeat if desired.

Inactive ingredients

Water (Aqua), Sodium Laureth Sulfate, Sodium Chloride, Cocamide MEA, Glycol Distearate, Dimethicone, Acrylates Copolymer, Glycerin, Cocamidopropyl Betaine, Fragrance (Parfum), Laureth-4, Guar Hydroxypropyltrimonium Chlorie, Sodium Hydroxide, Tetrasodium EDDTA, Methylchloroisothiazolinone, Methylisothiazolinone.